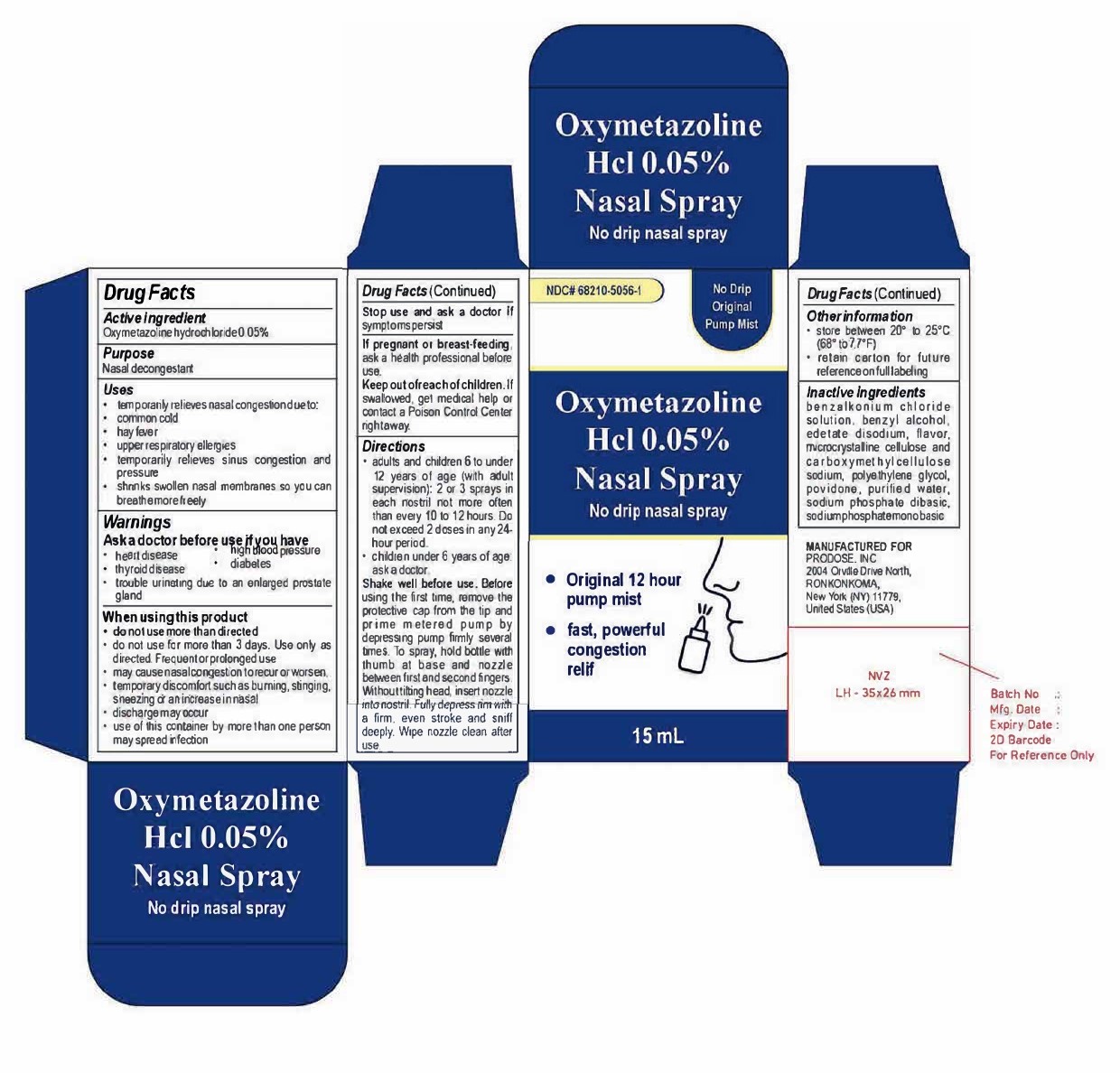 DRUG LABEL: Oxymetazoline hydrochloride
NDC: 68210-5056 | Form: SPRAY
Manufacturer: Prodose, Inc.
Category: otc | Type: HUMAN OTC DRUG LABEL
Date: 20260211

ACTIVE INGREDIENTS: OXYMETAZOLINE HYDROCHLORIDE 0.05 g/100 mL
INACTIVE INGREDIENTS: BENZALKONIUM CHLORIDE; EDETATE DISODIUM; CARBOXYMETHYLCELLULOSE SODIUM; WATER; CELLULOSE, MICROCRYSTALLINE; SODIUM PHOSPHATE, DIBASIC; SODIUM PHOSPHATE, MONOBASIC; BENZYL ALCOHOL; POLYETHYLENE GLYCOL, UNSPECIFIED; POVIDONE

Oxymetazoline Hydrochloride 0.05% Nasal Spray

Active ingredient

Oxymetazoline hydrochloride 0.05%

Purpose

Nasal decongestant

Uses

- temporarily relieves nasal congestion due to:

- common cold
- hay fever
- upper respiratory allergies

- temporarily relieves sinus congestion and pressure

shrinks swollen nasal membranes so you can breathe more freely

Warnings

Ask a doctor before use if you have

- heart disease
- high blood pressure
- thyroid disease
- diabetes
- trouble urinating due to an enlarged prostate gland

When using this product

- do not use more than directed
- do not use for more than 3 days. Use only as directed. Frequent or prolonged use may cause nasal congestion to recur or worsen.
- temporary discomfort such as burning, stinging, sneezing or an increase in nasal discharge may occur
- use of this container by more than one person may spread infection

Stop use and ask a doctor if symptoms persist

PREGNANCY OR BREAST FEEDING

If pregnant or breast-feeding, ask a health professional before use.

Keep out of reach of children. If swallowed, get medical help or contact a Poison Control Center right away.

Directions

- adults and children 6 to under 12 years of age (with adult supervision): 2 or 3 sprays in each nostril not more often than every 10 to 12 hours. Do not exceed 2 doses in any 24-hour period.
- children under 6 years of age: ask a doctor.

Shake well before use. Before using the first time, remove the protective cap from the tip and prime metered pump by depressing pump firmly several times. To spray, hold bottle with thumb at base and nozzle between first and second fingers. Without tilting head, insert nozzle into nostril. Fully depress rim with a firm, even stroke and sniff deeply. Wipe nozzle clean after use.

Other information

- store between 20° to 25°C (68° to 77°F)
- retain carton for future reference on full labelling

Inactive ingredients

benzalkonium chloride solution, benzyl alcohol, edetate disodium, flavor, microcrystalline cellulose and carboxymethylcellulose sodium, polyethylene glycol, povidone, purified water, sodium phosphate dibasic, sodium phosphate monobasic